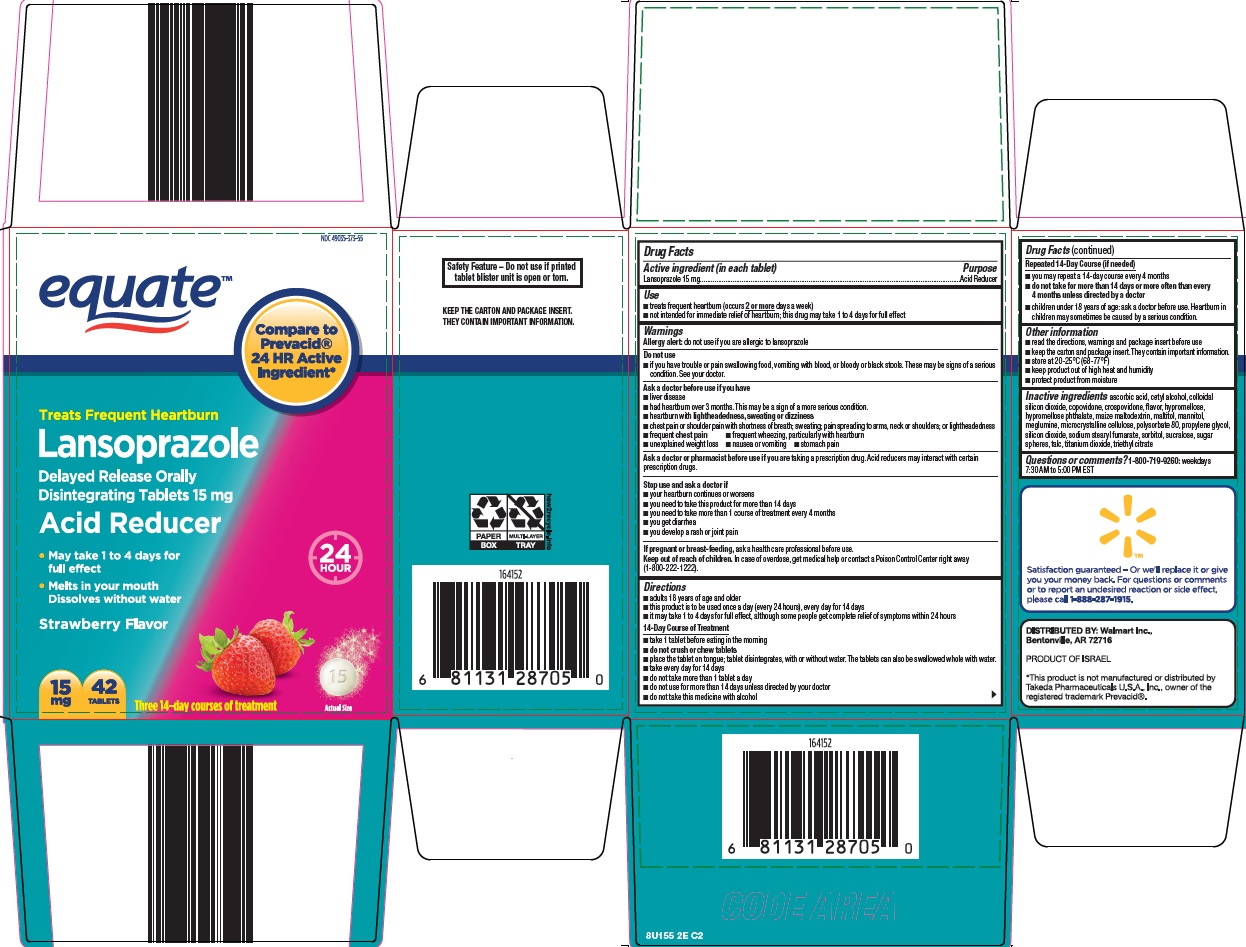 DRUG LABEL: equate lansoprazole
NDC: 49035-373 | Form: TABLET, ORALLY DISINTEGRATING, DELAYED RELEASE
Manufacturer: Wal-Mart Stores Inc
Category: otc | Type: HUMAN OTC DRUG LABEL
Date: 20221207

ACTIVE INGREDIENTS: LANSOPRAZOLE 15 mg/1 1
INACTIVE INGREDIENTS: ASCORBIC ACID; CETYL ALCOHOL; SILICON DIOXIDE; COPOVIDONE K25-31; CROSPOVIDONE (15 MPA.S AT 5%); HYPROMELLOSE, UNSPECIFIED; MALTITOL; MANNITOL; MEGLUMINE; MICROCRYSTALLINE CELLULOSE; POLYSORBATE 80; PROPYLENE GLYCOL; SODIUM STEARYL FUMARATE; SORBITOL; SUCRALOSE; TALC; TITANIUM DIOXIDE; TRIETHYL CITRATE

Wal-Mart Lansoprazole Drug Facts

Active ingredient (in each tablet)

Lansoprazole 15 mg

Purpose

Acid Reducer

Use

- treats frequent heartburn (occurs 2 or more days a week)
- not intended for immediate relief of heartburn; this drug may take 1 to 4 days for full effect

Warnings

Allergy alert: do not use if you are allergic to lansoprazole

Do not use

if you have trouble or pain swallowing food, vomiting with blood, or bloody or black stools. These may be signs of a serious condition. See your doctor.

Ask a doctor before use if you have

- liver disease
- had heartburn over 3 months. This may be a sign of a more serious condition.
- heartburn with lightheadedness, sweating or dizziness
- chest pain or shoulder pain with shortness of breath; sweating; pain spreading to arms, neck or shoulders; or lightheadedness
- frequent chest pain
- frequent wheezing, particularly with heartburn
- unexplained weight loss
- nausea or vomiting
- stomach pain

Ask a doctor or pharmacist before use if you are

taking a prescription drug. Acid reducers may interact with certain prescription drugs.

Stop use and ask a doctor if

- your heartburn continues or worsens
- you need to take this product for more than 14 days
- you need to take more than 1 course of treatment every 4 months
- you get diarrhea
- you develop a rash or joint pain

If pregnant or breast-feeding,

ask a health professional before use.

Keep out of reach of children.

In case of overdose, get medical help or contact a Poison Control Center right away (1-800-222-1222).

Directions

- adults 18 years of age and older
- this product is to be used once a day (every 24 hours), every day for 14 days
- it may take 1 to 4 days for full effect, although some people get complete relief of symptoms within 24 hours

14-Day Course of Treatment

- take 1 tablet before eating in the morning
- do not crush or chew tablets
- place the tablet on tongue; tablet disintegrates, with or without water. The tablets can also be swallowed whole with water.
- take every day for 14 days
- do not take more than 1 tablet a day
- do not use for more than 14 days unless directed by your doctor
- do not take this medicine with alcohol

Repeated 14-Day Course (if needed)

- you may repeat a 14-day course every 4 months
- do not take for more than 14 days or more often than every 4 months unless directed by a doctor
- children under 18 years of age: ask a doctor before use. Heartburn in children may sometimes be caused by a serious condition.

Other information

- read the directions, warnings and package insert before use
- keep the carton and package insert. They contain important information.
- store at 20-25°C (68-77°F)
- keep product out of high heat and humidity
- protect product from moisture

Inactive ingredients

ascorbic acid, cetyl alcohol, colloidal silicon dioxide, copovidone, crospovidone, flavor, hypromellose, hypromellose phthalate, maize maltodextrin, maltitol, mannitol, meglumine, microcrystalline cellulose, polysorbate 80, propylene glycol, silicon dioxide, sodium stearyl fumarate, sorbitol, sucralose, sugar spheres, talc, titanium dioxide, triethyl citrate

Questions or comments?

1-800-719-9260: weekdays 7:30 AM to 5:00 PM EST

Consumer Information

Treats Frequent Heartburn

Lansoprazole

Delayed Release

Orally Disintegrating Tablets 15 mg

acid reducer

• May take 1 to 4 days for full effect

Please read the entire package insert before taking

Lansoprazole Delayed Release Orally Disintegrating Tablets.

Save for future reference.

How Lansoprazole delayed release orally disintegrating tablets Treats Your Frequent Heartburn

Lansoprazole delayed release orally disintegrating tablets stops acid production at the source - the pumps that release acid into the stomach. Lansoprazole delayed release orally disintegrating tablet is taken once a day (every 24 hours), every day for 14 days.

What You Can Expect When Taking Lansoprazole delayed release orally disintegrating tablets

Frequent heartburn can occur anytime during the 24-hour period (day or night). Take Lansoprazole delayed release orally disintegrating tablets in the morning before eating. Lansoprazole is clinically proven to treat frequent heartburn. Although some people get complete relief of symptoms within 24 hours, it may take 1 to 4 days for full effect. Make sure you take Lansoprazole delayed release orally disintegrating tablets every day for 14 days to treat your frequent heartburn.

Who Should Take Lansoprazole delayed release orally disintegrating tablets

Adults (18 years and older) with frequent heartburn - when you have heartburn 2 or more days a week.

Who Should NOT Take Lansoprazole delayed release orally disintegrating tablets

People who have one episode of heartburn a week or less, or who want immediate relief of heartburn.

How to Take Lansoprazole delayed release orally disintegrating tablets

14-DAY Course of Treatment

- Take 1 tablet before eating in the morning.
- Do not crush or chew tablets.
- Place the tablet on tongue; tablet disintegrates, with or without water. The tablets can also be swallowed whole with water.
- Take every day for 14 days.
- Do not take more than 1 tablet a day.
- Do not use for more than 14 days unless directed by your doctor.
- Do not take this medicine with alcohol.

When to Take Lansoprazole delayed release orally disintegrating tablets Again

You may repeat a 14-day course of therapy every 4 months.

When to Talk to Your Doctor

Do not take for more than 14 days or more often than every 4 months unless directed by a doctor.

Warnings and When to Ask Your Doctor

Allergy alert: Do not use if you are allergic to lansoprazole

Do not use

- if you have trouble or pain swallowing food, vomiting with blood, or bloody or black stools. These may be signs of a serious condition. See your doctor.

Ask a doctor before use if you have

- liver disease
- had heartburn over 3 months. This may be a sign of a more serious condition.
- heartburn with lightheadedness, sweating or dizziness
- chest pain or shoulder pain with shortness of breath; sweating; pain spreading to arms, neck or shoulders; or lightheadedness
- frequent chest pain
- frequent wheezing, particularly with heartburn
- unexplained weight loss
- nausea or vomiting
- stomach pain

Ask a doctor or pharmacist before use if you are

taking

- warfarin (blood-thinning medicine)
- prescription antifungal or anti-yeast medicines
- digoxin (heart medicine)
- theophylline (asthma medicine)
- tacrolimus or mycophenolate mofetil (immune system medicines)
- atazanavir (medicine for HIV infection)
- methotrexate (arthritis medicine)

Stop use and ask a doctor if

- your heartburn continues or worsens
- you need to take this product for more than 14 days
- you need to take more than 1 course of treatment every 4 months
- you get diarrhea
- you develop a rash or joint pain

If pregnant or breast-feeding, ask a health care professional before use.

Keep out of reach of children.

In case of overdose, get medical help or contact a Poison Control Center right away (1-800-222-1222).

Tips for Managing Heartburn

- Avoid foods or drinks that are more likely to cause heartburn, such as rich, spicy, fatty and fried foods, chocolate, caffeine, alcohol and even some acidic fruits and vegetables.
- Eat slowly and do not eat big meals.
- Do not eat late at night or just before bedtime.
- Do not lie flat or bend over soon after eating.
- Raise the head of your bed.
- Wear loose-fitting clothing around your stomach.
- If you are overweight, lose weight.
- If you smoke, quit smoking.

Clinical studies prove that lansoprazole effectively treats frequent heartburn

In three clinical studies, lansoprazole was shown to be significantly better than placebo in treating frequent heartburn.

How Lansoprazole delayed release orally disintegrating tablets is Sold

This medicine is available in 14 tablet, 28 tablet and 42 tablet sizes. These sizes contain one, two and three 14-day courses of treatment, respectively. Do not use for more than 14 days in a row unless directed by your doctor. For the 28 count (two 14-day courses) and the 42 count (three 14-day courses), you may repeat a 14-day course every 4 months.

For Questions or Comments About Lansoprazole delayed release orally disintegrating tablets

Call 1-800-719-9260

weekdays 7:30 AM to 5:00 PM EST

Made in Israel

Manufactured by:

Dexcel Pharma Technologies Ltd.

10 Hakidma Street, Yokneam 2069200, Israel

:8U174 00 J3

Package/Label Principal Display Panel

equate™

Compare to Prevacid® 24 HR Active Ingredient

Treats Frequent Heartburn

Lansoprazole

Delayed Release Orally Disintegrating Tablets 15 mg

Acid Reducer

24 HOUR

May take 1 to 4 days for full effect

Melts in your mouth

Dissolves without water

Strawberry Flavor

15 mg

42 TABLETS

Three 14-day courses of treatment

Actual Size